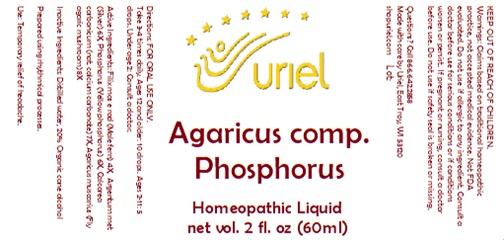 DRUG LABEL: Agaricus comp. Phosphorus
NDC: 48951-1377 | Form: LIQUID
Manufacturer: Uriel Pharmacy, Inc.
Category: homeopathic | Type: HUMAN OTC DRUG LABEL
Date: 20241120

ACTIVE INGREDIENTS: PHOSPHORUS 6 [hp_X]/1 mL; SILVER 6 [hp_X]/1 mL; AMANITA MUSCARIA FRUITING BODY 8 [hp_X]/1 mL; OYSTER SHELL CALCIUM CARBONATE, CRUDE 7 [hp_X]/1 mL; DRYOPTERIS FILIX-MAS ROOT 4 [hp_X]/1 mL
INACTIVE INGREDIENTS: ALCOHOL; WATER

Agaricus comp. Phosphorus

INDICATIONS AND USAGE

Directions: FOR ORAL USE ONLY.

DOSAGE AND ADMINISTRATION

Take 3-4 times daily. Ages 12 and older: 10 drops. Ages 2-11: 5 drops. Under age 2: Consult a doctor.

ACTIVE INGREDIENT

Active Ingredients: Filix mas e rad (Male fern) 4X, Argentum met (Silver) 6X, Phosphorus (Yellow phosphorus) 6X, Calcarea carbonicum (nat.calcium carbonate) 7X, Agaricus muscarius (Fly agaric mushroom) 8X

Inactive Ingredients: Distilled water, 20% Organic cane alcohol

Prepared using rhythmical processes.

PURPOSE

Use: Temporary relief of headache.

KEEP OUT OF REACH OF CHILDREN.

WARNINGS

Warnings: Claims based on traditional homeopathic practice, not accepted medical evidence. Not FDA evaluated. Do not use if allergic to any ingredient. Consult a doctor before use for serious conditions or if conditions worsen or persist. If pregnant or nursing, consult a doctor before use. Do not use if safety seal is broken or missing.

Questions? Call 866.642.2858
Made with care by Uriel, East Troy, WI 53120
shopuriel.com Lot: